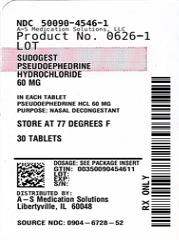 DRUG LABEL: Pseudoephedrine Hydrochloride
NDC: 50090-4546 | Form: TABLET
Manufacturer: A-S Medication Solutions
Category: otc | Type: HUMAN OTC DRUG LABEL
Date: 20250424

ACTIVE INGREDIENTS: PSEUDOEPHEDRINE HYDROCHLORIDE 60 mg/1 1
INACTIVE INGREDIENTS: LACTOSE MONOHYDRATE; CROSCARMELLOSE SODIUM; SILICA; CELLULOSE, MICROCRYSTALLINE; MAGNESIUM STEARATE; STEARIC ACID

1215-Major

Drug Facts

Active ingredient (in each tablet)

Pseudoephedrine HCl 60 mg

Purpose

Nasal decongestant

Uses

- temporarily relieves nasal congestion due to the common cold, hay fever or other upper respiratory allergies
- temporarily relieves sinus congestion and pressure

WARNINGS

Do not use if you are now taking a prescription monoamine oxidase inhibitor (MAOI) (certain drugs for depression, psychiatric or emotional conditions, or Parkinson’s disease), or for 2 weeks after stopping the MAOI drug. If you do not know if your prescription drug contains an MAOI, ask a doctor or pharmacist before taking this product.

Ask a doctor before use if you have

- diabetes
- heart disease
- high blood pressure
- thyroid disease
- trouble urinating due to an enlarged prostate gland

When using this product do not exceed recommended dose.

Stop use and ask a doctor if

- nervousness, dizziness, or sleeplessness occur
- symptoms do not improve within 7 days or occur with a fever

PREGNANCY OR BREAST FEEDING

If pregnant or breast-feeding, ask a health professional before use.

Keep out of reach of children.

OVERDOSAGE

In case of overdose, get medical help or contact a Poison Control Center right away.

Directions

- adults and children 12 years and older: take 1 tablet every 4 to 6 hours. Do not take more than 4 tablets in 24 hours.
- children under 12 years of age: do not use

Other information

- store in a dry place at 15° – 30°C (59° – 86°F)
- use by expiration date on package

INACTIVE INGREDIENT

croscarmellose sodium, lactose, magnesium stearate, microcrystalline cellulose, silica and stearic acid.

Questions or comments?

(800) 231-4670

TAMPER EVIDENT: DO NOT USE IF IMPRINTED SAFETY SEAL UNDER CAP IS BROKEN OR MISSING

DISTRIBUTED BY: MAJOR® PHARMACEUTICALS
INDIANAPOLIS, IN 46268
www.majorpharmaceuticals.com